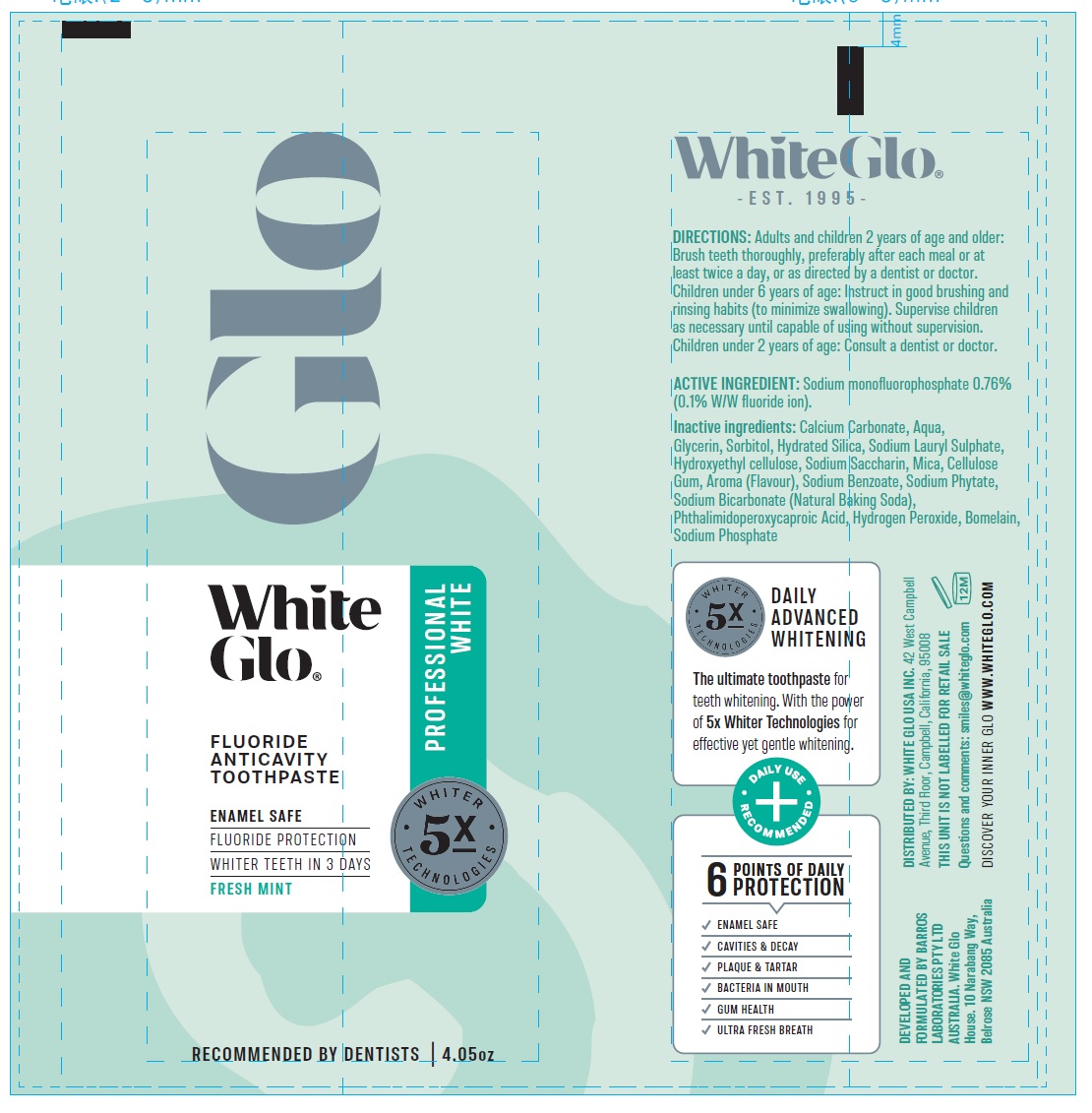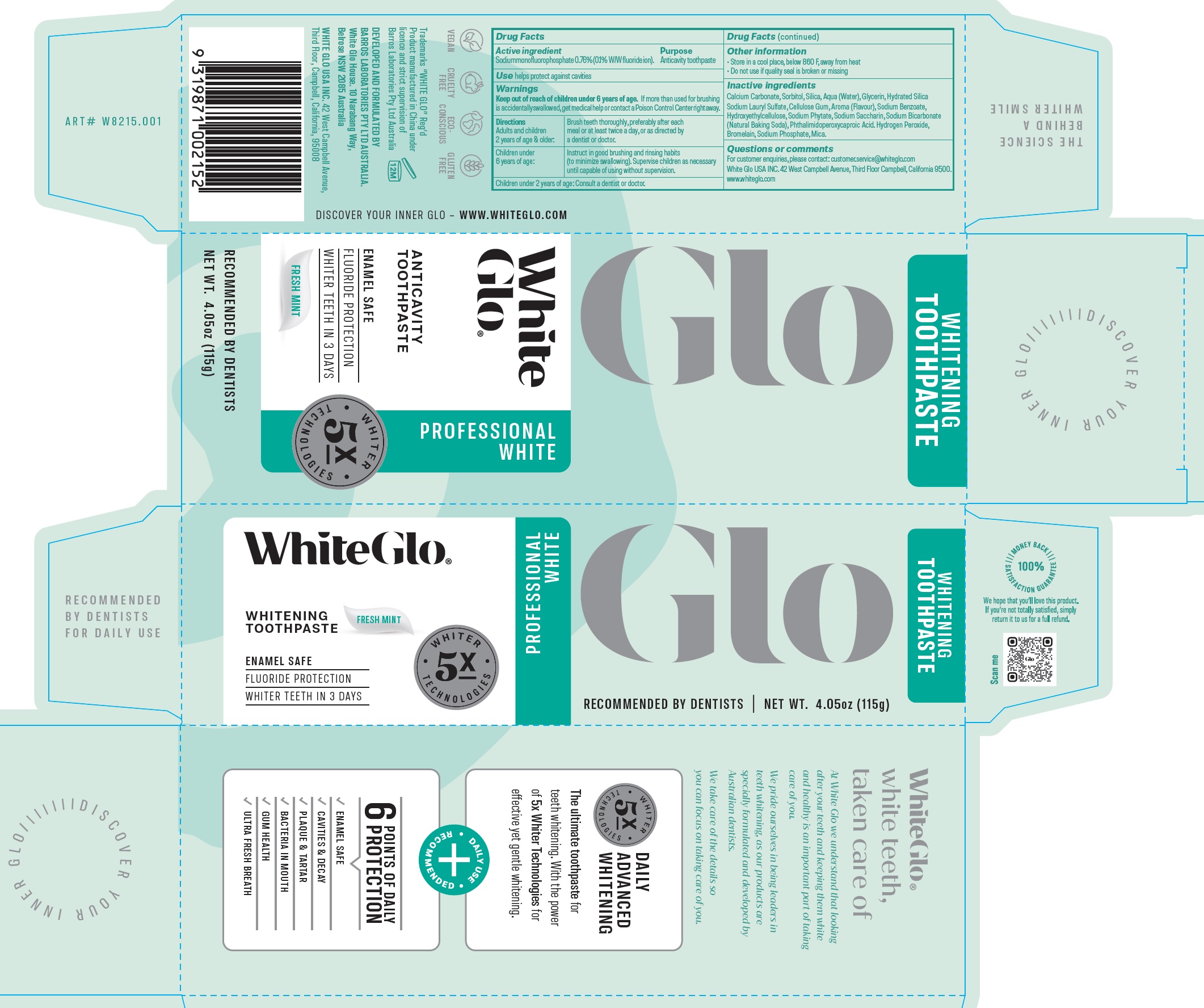 DRUG LABEL: White Glo Professional White AntiCavity
NDC: 73656-019 | Form: PASTE, DENTIFRICE
Manufacturer: WHITE GLO USA INC
Category: otc | Type: HUMAN OTC DRUG LABEL
Date: 20250226

ACTIVE INGREDIENTS: SODIUM FLUORIDE 1 mg/1 g
INACTIVE INGREDIENTS: CALCIUM CARBONATE; SORBITOL; SILICON DIOXIDE; WATER; GLYCERIN; CARBOXYMETHYLCELLULOSE SODIUM, UNSPECIFIED; SODIUM BENZOATE; HYDROXYETHYL CELLULOSE, UNSPECIFIED; PHYTATE SODIUM; SACCHARIN SODIUM; SODIUM BICARBONATE; PHTHALIMIDOPEROXYCAPROIC ACID; HYDROGEN PEROXIDE; BROMELAINS; SODIUM PHOSPHATE; MICA

White Glo Professional White AntiCavity Toothpaste

Active ingredient

Sodium monofluorophosphate0.76% (0.1% W/W fluoride ion).

Purpose

Anticavity toothpaste

Use

helps protect against cavities

Warnings

Keep out of reach of children

If more than used for brushing is accidentally swallowed, get medical help or contact a Poison Control Center right away. under 6 years of age.

Directions

Adults and children 2 years of age & older: | Brush teeth thoroughly, preferably after each meal or at least twice a day, or as directed by a dentist or doctor.
Children under 6 years of age: | Instruct in good brushing and rinsing habits (to minimize swallowing). Supervise children as necessary until capable of using without supervision.

Consult a dentist or doctor. Children under 2 years of age:

Other information

• Store in a cool place, below 860 F, away from heat • Do not use if quality seal is broken or missing

Inactive ingredients

Calcium Carbonate, Sorbitol, Silica, Aqua (Water), Glycerin, Hydrated Silica Sodium Lauryl Sulfate, Cellulose Gum, Aroma (Flavour), Sodium Benzoate, Hydroxyethylcellulose, Sodium Phytate, Sodium Saccharin, Sodium Bicarbonate (Natural Baking Soda), Phthalimidoperoxycaproic Acid. Hydrogen Peroxide, Bromelain, Sodium Phosphate, Mica.

Questions or comments

For customer enquiries, please contact: customer.service@whiteglo.com White Glo USA INC. 42 West Campbell Avenue, Third Floor Campbell, California 9500. www.whiteglo.com